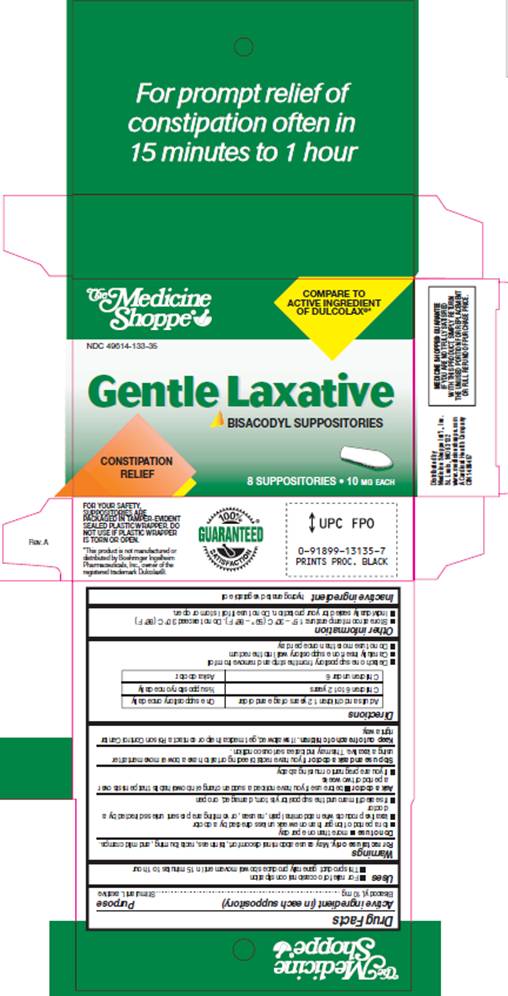 DRUG LABEL: Bisacodyl Laxative
NDC: 49614-133 | Form: SUPPOSITORY
Manufacturer: Medicine Shoppe International Inc
Category: otc | Type: HUMAN OTC DRUG LABEL
Date: 20100312

ACTIVE INGREDIENTS: bisacodyl 10 mg/1 1
INACTIVE INGREDIENTS: fat, hard

DRUG FACTS

ACTIVE INGREDIENT (in each suppository)

Bisacodyl, 10 mg

PURPOSE

Stimulant Laxative

USES

- For relief of occasional constipation
- This product generally produces bowel movement in 15 minutes to 1 hour

WARNINGS

For rectal use only. May cause abdominal discomfort, faintness, rectal burning, and mild cramps.

Do not use

- more than one per day
- for a period of longer than one week unless directed by a doctor
- laxative products when abdominal pain, nausea, or vomiting are present unless directed by a doctor
- if seal under product lid is torn, damaged, or open

Ask a doctor before use

- if you have noticed a sudden change in bowel habits that persist over a period of two weeks
- if you are pregnant or nursing a baby

Stop use and ask a doctor

if you have rectal bleeding or fail to have a bowel movement after using a laxative. This may indicate a serious condition.

Keep out of reach of children

If swallowed, get medical help or contact a Poison Control Center right away.

DIRECTIONS

Adults and children 12 years of age and older | One suppository once daily
Children 6 to 12 years | 1/2 suppository once daily
Children under 6 | Ask a doctor

- Detach one suppository from the strip and remove from foil
- Carefully insert one suppository well into the rectum
- Do not use more than once per day

OTHER INFORMATION

- Store at room temperature: 15°- 30° C (59° - 86° F). Do not exceed 30° C (86° F).
- Individually sealed for your protection. Do not use if foil is torn or open.

INACTIVE INGREDIENT

hydrogenated vegetable oil

PACKAGE INFORMATION

The Medicine Shoppe®
COMPARE TO ACTIVE INGREDIENT OF DULCOLAX®*
NDC 49614-133-35

Gentle Laxative

BISACODYL SUPPOSITORIES
CONSTIPATION RELIEF
8 SUPPOSITORIES 10 MG EACH

FOR YOUR SAFETY, SUPPOSITORIES ARE PACKAGED IN PAMPER-EVIDENT SEALED PLASTIC WRAPPER. DO NOT USE IF PLASTIC WRAPPER IS TORN OR OPEN.
*This product is not manufactured or distributed by Boehringer Ingelhem
Pharmaceuticals, Inc., owner of the registered trademark Dulcolax®.

Another Quality Product
Distributed by Medicine Shoppe Int'l., Inc.
St. Louis, MO 63132
www.medicineshoppe.com
A Cardinal Health Company